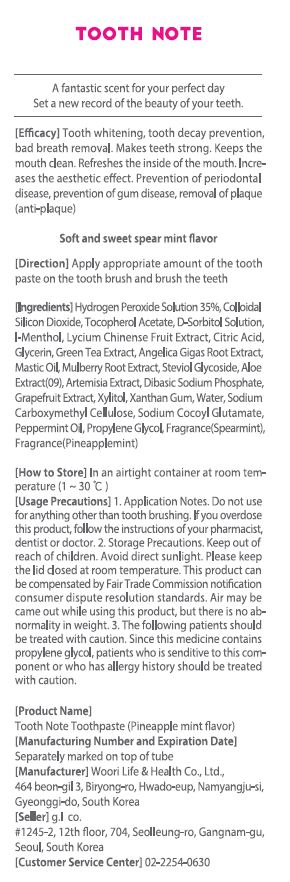 DRUG LABEL: TOOTH NOTE PINEAPPLE MINT
NDC: 73065-0002 | Form: PASTE, DENTIFRICE
Manufacturer: WOORILIFE&HEALTH
Category: otc | Type: HUMAN OTC DRUG LABEL
Date: 20210412

ACTIVE INGREDIENTS: SILICON DIOXIDE 2.14 g/100 g
INACTIVE INGREDIENTS: XYLITOL; WATER

ACTIVE INGREDIENT

SILICON DIOXIDE

PURPOSE

Tooth whitening, tooth deay prevention, bod breath removal. Makes teeth strong. Keeps the mouth c;ean. Refreshes the Inside of the mouth. Increases the aesthetic effect. Prevention of gum disease, removal of plaque (ant-plaque)

Keep out of reach of children

INDICATIONS AND USAGE

apply appropriate amount of the tooth paste on the tooth brush and brush the teeth

WARNINGS

Storage method

1. Keep it at room temperature in a classified container.

2. Cover and store at room temperature.

3. Store in a not moisture and cool place.

4. Air may come out during use of this product, but there is no problem with its weight.

Usage Precautions

1. Be careful not to swallow. Rinse mouth thoroughly after use

2. If the use of toothpaste causes abnormalities such as gums or mouth injury, discontinue use and consult a doctor or dentist.

3. For children under 6 years of age, use a small amount of toothpaste as small as pea per use, and use under the guidance of a guardian to avoid sucking or swallowing.

4. If a child under 6 years old swallows large amount, consult with a doctor or dentist immediately.

5. Keep out of the reach of children under 6 years of age.

INACTIVE INGREDIENT

hydrogen peroxide, tocopherol acetate, d-sorbitol, propylene glycol, etc.

DOSAGE AND ADMINISTRATION

For dental use only